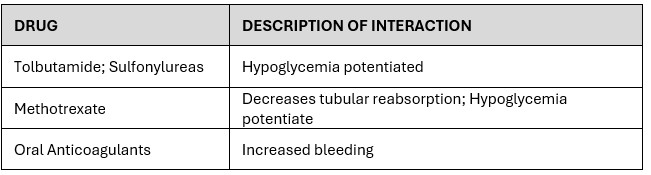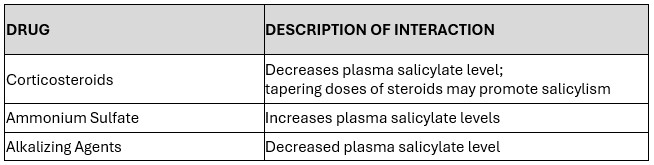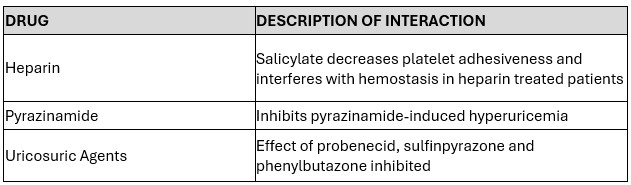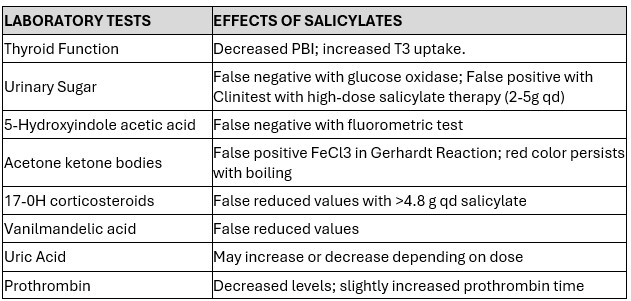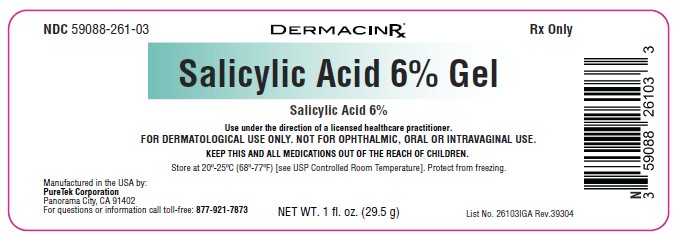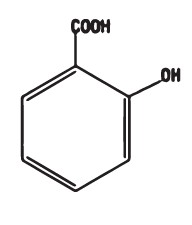 DRUG LABEL: Salicylic Acid 6% Gel
NDC: 59088-261 | Form: GEL
Manufacturer: PureTek Corporation
Category: prescription | Type: HUMAN PRESCRIPTION DRUG LABEL
Date: 20260206

ACTIVE INGREDIENTS: SALICYLIC ACID 6 g/100 g
INACTIVE INGREDIENTS: SODIUM ASCORBYL PHOSPHATE; SODIUM HYALURONATE; CALCIUM PANTOTHENATE; CARTHAMUS TINCTORIUS (SAFFLOWER) OLEOSOMES; PYRIDOXINE HCL; PROPYLENE GLYCOL; ROSA DAMASCENA FLOWER OIL; VETIVERIA ZIZANOIDES ROOT OIL; AQUA; CANANGA ODORATA FLOWER OIL; CAPRYLYL GLYCOL; PHENOXYETHANOL; SODIUM HYDROXIDE; DIMETHICONE; DIMETHICONE CROSSPOLYMER; ETHYLHEXYLGLYCERIN; GLYCERIN; HEXYLENE GLYCOL; HYDROXYETHYL CELLULOSE, UNSPECIFIED; LAVANDULA ANGUSTIFOLIA (LAVENDER) OIL; PEG-4; .ALPHA.-TOCOPHEROL ACETATE, DL-; FRAGRANCE 13576; SILICA; NIACINAMIDE; GINGER; BISABOLOL; MALTODEXTRIN

Salicylic Acid 6% Gel
(Salicylic Acid 6%)
Rx Only
FOR DERMATOLOGICAL USE ONLY. NOT FOR OPHTHALMIC, ORAL OR INTRAVAGINAL USE.

Active Ingredient

Salicylic Acid 6%

INACTIVE INGREDIENTS

Salicylic Acid 6% Gel contains 60 mg of salicylic acid per gram in a vehicle composed of Aqua (Purified Water), Cananga Odorata Flower Oil, Caprylyl Glycol, Dimethicone, Dimethicone Crosspolymer, Ethylhexylglycerin, Fragrance, GenRx Complex® ([consisting of: Bisabolol, Calcium Pantothenate (Vitamin B5), Carthamus Tinctorius (Safflower) Oleosomes, Maltodextrin, Niacinamide (Vitamin B3), Pyridoxine HCl (Vitamin B6), Silica, Sodium Ascorbyl Phosphate (Vitamin C), Sodium Hyaluronate, Sodium Starch Octenylsuccinate, DL-Alpha Tocopheryl Acetate (Vitamin E), Zingiber Officinale (Ginger) Root Extract]), Glycerin, Hexylene Glycol, Hydroxyethyl Cellulose, Lavandula Angustifolia (Lavender) Oil, PEG-4, Phenoxyethanol, Propylene Glycol, Rosa Damascena Flower Oil, Sodium Hydroxide, Vetiveria Zizanoides Root Oil.

CHEMICAL STRUCTURE

Salicylic acid is the 2-hydroxy derivative of benzoic acid having the following structure:

CLINICAL PHARMACOLOGY

Salicylic acid has been shown to produce desquamation of the horny layer of skin while not affecting qualitative or quantitative changes in the structure of the viable epidermis. The mechanism of action has been attributed to the dissolution of intercellular cement substances. In a study of the percutaneous absorption of salicylic acid in a 6% salicylic acid gel in four patients with extensive active psoriasis, Taylor and Halprin showed that the peak serum salicylate levels never exceeded 5 mg/100 ml even though more than 60% of the applied salicylic acid was absorbed. Systemic toxic reactions are usually associated with much higher serum levels (30 to 40 mg/100 ml). Peak serum levels occurred within 5 hours of the topical application under occlusion. The sites were occluded for 10 hours over the entire body surface below the neck. Since salicylates are distributed in the extracellular space, patients with a contracted extracellular space due to dehydration or diuretics have higher salicylate levels than those with a normal extracellular space (See PRECAUTIONS).
The major metabolites identified in the urine after topical administration are salicylic acid (52%), salicylate glucuronides (42%) and free salicylic acid (6%). The urinary metabolites after percutaneous absorption differ from those after oral salicylate administration; those derived from percutaneous absorption contain more salicylate glucuronides and less salicyluric and salicylic acid. Almost 95% of a single dose of salicylate is excreted within 24 hours of its entrance into the extracellular space.

Fifty to eighty percent of salicylate is protein bound to albumin. Salicylates compete with the binding of several drugs and can modify the actions of these drugs. By similar competitive mechanisms other drugs can influence the serum levels of salicylate (See PRECAUTIONS).

INDICATIONS AND USAGE

For Dermatologic Use: Salicylic Acid 6% Gel is a topical aid in the removal of excessive keratin in hyperkeratotic skin disorders including verrucae, and the various ichthyoses (vulgaris, sex-linked and lamellar), keratosis palmaris and plantaris keratosis pilaris, pityriasis rubra pilaris, and psoriasis (including body, scalp, palms and soles).

For Podiatric Use: Salicylic Acid 6% Gel is a topical aid in the removal of excessive keratin on dorsal and plantar hyperkeratotic lesions.

CONTRAINDICATIONS

Salicylic Acid 6% Gel should not be used in any patient known to be sensitive to salicylic acid or any other listed ingredients. Salicylic Acid 6% Gel should not be used in children under 2 years of age.

WARNINGS

Prolonged use over large areas, especially in children and those patients with significant renal or hepatic impairment, could result in salicylism. Concomitant use of other drugs which may contribute to elevated serum salicylate levels should be avoided where the potential for toxicity is present. In children under12 years of age and those patients with renal or hepatic impairment, the area to be treated should be limited and the patient monitored closely for signs of salicylate toxicity: nausea, vomiting, dizziness, loss of hearing, tinnitus, lethargy, hyperpnea, diarrhea, and psychic disturbances. In the event of salicylic acid toxicity, the use of Salicylic Acid 6% Gel should be discontinued. Fluids should be administered to promote urinary excretion. Treatment with sodium bicarbonate (oral or intravenous) should be instituted as appropriate. Patients should be cautioned against the use of oral aspirin and other salicylate containing medications, such as sports injury creams, to avoid additional excessive exposure to salicylic acid.

Where needed, aspirin should be replaced by an alternative non-steroidal anti-inflammatory agent that is not salicylate based.

Patients should be advised not to apply occlusive dressings, clothing or other occlusive topical products such as petrolatum-based ointments to prevent excessive systemic exposure to salicylic acid. Excessive application of the product other than what is needed to cover the affected area will not result in a more rapid therapeutic benefit.

Due to potential risk of developing Reye's syndrome, salicylate products should not be used in children and teenagers with varicella or influenza, unless directed by a licensed health care practitioner.

PRECAUTIONS

Avoid contact with eyes, lips, broken or inflamated skin, and other mucous membranes.

DRUG INTERACTIONS

(The following interactions are from a published review and include reports concerning both oral and topical salicylate administration. The relationship of these interactions to the use of Salicylic Acid 6% Gel is not known).

I. Due to the competition of salicylate with other drugs for binding to serum albumin the following drug interactions may occur:

II. Drugs changing salicylate levels by altering renal tubular reabsorption:

III. Drugs with complicated interactions with salicylates:

The following alterations of laboratory tests have been reported during salicylate therapy:

Pregnancy: (Category C) - Salicylic acid has been shown to be teratogenic in rats and monkeys. It is difficult to extrapolate from oral doses of acetylsalicylic acid used in these studies to topical administration as the oral dose to monkeys may represent 4 times the maximal daily human dose of salicylic acid when applied topically over a large body surface. There are no adequate and well- controlled studies in pregnant women. Salicylic Acid 6% Gel should be used during pregnancy only if the potential benefit justifies the potential risk to the fetus.

Nursing Mothers: Because of the potential for serious adverse reactions in nursing infants from the mother's use of Salicylic Acid 6% Gel, a decision should be made whether to discontinue nursing or to discontinue the drug, taking into account the importance of the drug to the mother. If used by nursing mothers, it should not be used on the chest area to avoid accidental contamination of the child.

Carcinogenesis, Mutagenesis, Impairment of Fertility: No data is available concerning potential carcinogenic or reproductive effects of Salicylic Acid 6% Gel. It has been shown to lack mutagenic potential in the Ames Salmonella test.

KEEP THIS AND ALL MEDICATIONS OUT OF THE REACH OF CHILDREN.

ADVERSE REACTIONS

Excessive erythema and scaling conceivably could result from use on open skin lesions. Call your licensed healthcare practitioner for medical advice about side effects.

OVERDOSAGE

See Warnings

DOSAGE AND ADMINISTRATION

The preferable method of use is to apply Salicylic Acid 6% Gel thoroughly to the affected area and to cover the treated area at night after washing and before retiring. Preferably, the skin should be hydrated for at least five minutes prior to application. The medication is washed off in the morning, and if excessive drying and/or irritation is observed, a bland cream or lotion may be applied. Once clearing is apparent, the occasional use of Salicylic Acid 6% Gel will usually maintain the remission. In those areas where occlusion is difficult or impossible, application may be made more frequently, hydration by wet packs or baths prior to application apparently enhances the effect (See WARNINGS). Unless hands are being treated, hands should be rinsed thoroughly after application. Excessive repeated application of Salicylic Acid 6% Gel will not necessarily increase its therapeutic benefit, but could result in increased local intolerance and systemic adverse effects such as salicylism.

HOW SUPPLIED

Salicylic Acid 6% Gel is available in 1 fl. oz. (29.5 g) tube NDC 59088-261-03

Store at 20°-25°C (68°-77°F) [see USP Controlled Room Temperature].

Protect from freezing and excessive heat. Keep container tightly closed.

All prescription substitutions using this product shall be made subject to state and federal statutes as applicable.

NOTE: This is not an Orange Book product and has not been subjected to FDA therapeutic equivalency or other equivalency testing. No representation is made as to generic status or bioequivalency. Each person recommending a prescription substitution using this product shall make such recommendations based on each person's professional opinion and knowledge, upon evaluating the active ingredients, excipients, inactive ingredients,and chemical formulation information provided herein.

For use on the order of a licensed healthcare practitioner. Call your doctor about side effects. To report side effects, call PureTek Corporation at 1-877-921-7873.
Manufactured in the USA by:
PureTek Corporation
Panorama City, CA 91402
For questions or information
Call toll-free: 877-921-7873